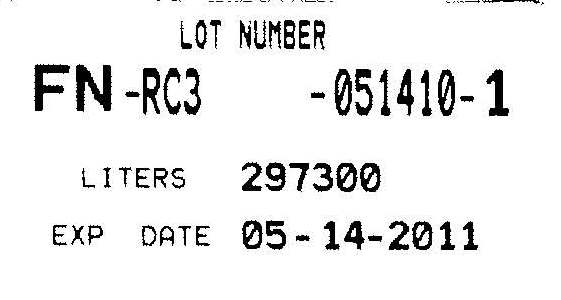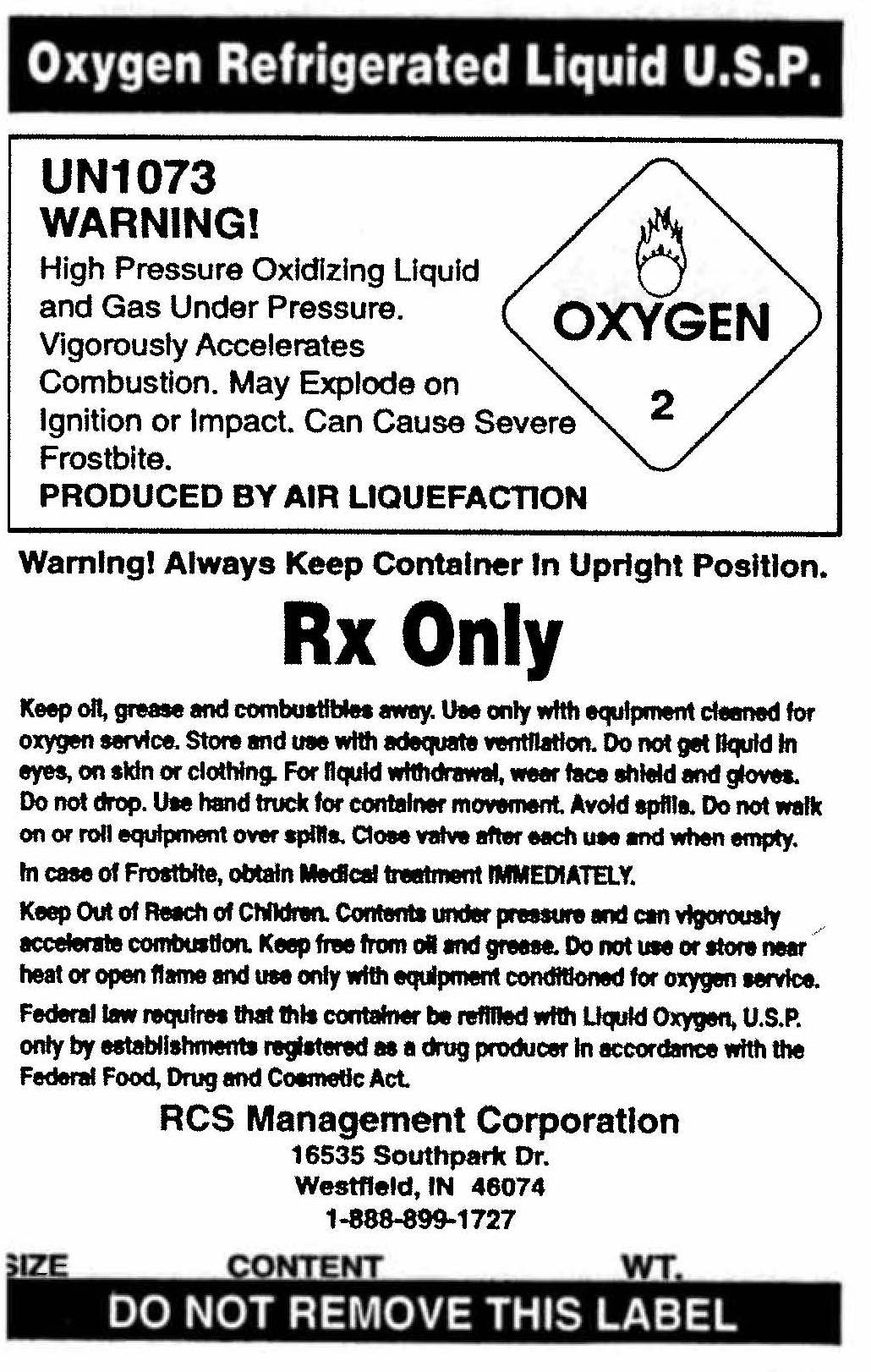 DRUG LABEL: Oxygen
NDC: 65864-001 | Form: GAS
Manufacturer: RCS Management Corporation
Category: prescription | Type: HUMAN PRESCRIPTION DRUG LABEL
Date: 20100528

ACTIVE INGREDIENTS: Oxygen 99 L/100 L

Oxygen